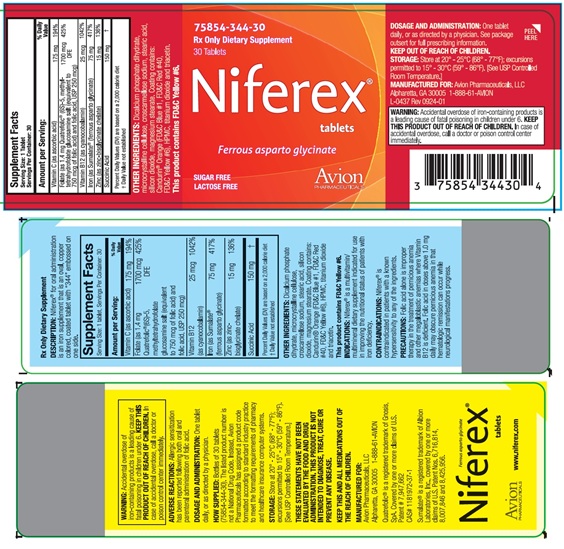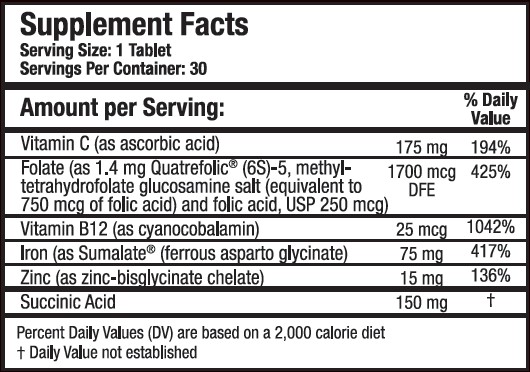 DRUG LABEL: Niferex
NDC: 75854-344 | Form: TABLET
Manufacturer: Avion Pharmaceuticals, LLC
Category: prescription | Type: HUMAN PRESCRIPTION DRUG LABEL
Date: 20250408

ACTIVE INGREDIENTS: FERROUS ASPARTO GLYCINATE 75 mg/1 1; ASCORBIC ACID 175 mg/1 1; LEVOMEFOLATE GLUCOSAMINE 750 ug/1 1; FOLIC ACID 250 ug/1 1; CYANOCOBALAMIN 25 ug/1 1; ZINC 15 mg/1 1; SUCCINIC ACID 150 mg/1 1
INACTIVE INGREDIENTS: CALCIUM PHOSPHATE, DIBASIC, DIHYDRATE; CELLULOSE, MICROCRYSTALLINE; CROSCARMELLOSE SODIUM; MAGNESIUM STEARATE; STEARIC ACID; SILICON DIOXIDE; FD&C BLUE NO. 1; FD&C RED NO. 40; FD&C YELLOW NO. 6; HYDROXYPROPYL METHYLCELLULOSE; TITANIUM DIOXIDE; TRIACETIN

Iron Supplement
Niferex® Tablets

Rx Only Dietary Supplement

DESCRIPTION

DESCRIPTION: Niferex® for oral administration is an iron supplement that is an oval, copper colored, coated tablet with "344" embossed on one side.

INACTIVE INGREDIENT

OTHER INGREDIENTS: Discalcium phosphate dihydrate, microcrystalline cellulose, croscarmellose sodium, stearic acid, silicon dioxide, magnesium stearate. Coating contains: Candurin® Orange (FD&C Blue #1, FD&C Red #40, FD&C Yellow #6), HPMC, titanium dioxide and triacetin.

This product contains FD&C Yellow #6.

INDICATIONS AND USAGE

INDICATIONS: Niferex® is a multivitamin/multimineral dietary supplement indicated for use in improving the nutritional status of patients with iron deficiency.

CONTRAINDICATIONS

CONTRAINDICATIONS: Niferex® is contraindicated in patients with a known hypersensitivity to any of the ingredients.

PRECAUTIONS

PRECAUTIONS: Folic acid alone is improper therapy in the treatment of pernicious anemia and other megaloblastic anemias where Vitamin B12 is deficient. Folic acid in doses above 1.0 mg daily may obscure pernicious anemia in that hematologic remission can occur while neurological manifestations progress.

BOXED WARNING

WARNING: Accidental overdose of iron-containing products is a leading cause of fatal poisoning in children under 6. KEEP THIS PRODUCT OUT OF REACH OF CHILDREN. In case of accidental overdose, call a doctor or poison control center immediately.

ADVERSE REACTIONS

ADVERSE REACTIONS: Allergic sensitization has been reported following both oral and parenteral administration of folic acid.

DOSAGE AND ADMINISTRATION: One tablet daily, or as directed by a physician.

HOW SUPPLIED

HOW SUPPLIED: Bottles of 30 tablets (75854-344-30). The listed product number is not a National Drug Code. Instead, Avion Pharmaceuticals has assigned a product code formatted according to standard industry practice to meet the formatting requirements of pharmacy and healthcare insurance computer systems.

STORAGE AND HANDLING

STORAGE: Store at 20° - 25°C (68° - 77°F); excursions permitted to 15° - 30°C (59° - 86°F) [See USP Controlled Room Temperature.]

THESE STATEMENTS HAVE NOT BEEN EVALUATED BY THE FOOD AND DRUG ADMINISTRATION. THIS PRODUCT IS NOT INTENDED TO DIAGNOSE, TREAT, CURE OR INTENDED TO DIAGNOSE, PREVENT ANY DISEASE.

KEEP THIS AND ALL MEDICATION OUT OF THE REACH OF CHILDREN.

MANUFACTURED FOR:

Avion Pharmaceuticals, LLC

Alpharetta, GA 30005 1-888-61-AVION
L-0437 Rev. 0924-01

Quatrefolic® is a registered trademark of Gnosis, SpA. Covered by one or more claims of U.S. Patent #7,947,662 CAS #1181972-37-1

Sumalate® is a registered trademark of Albion Laboratories, Inc., covered by one or more claims of U.S. Patent Nos. 6,716,814, 8,007,846 and 8,425,956.

PACKAGE LABEL

75854-344-30

Rx Only Dietary Supplement

30 Tablets

Sugar Free

Lactose Free

Niferex® Tablets (ferrous asparto glycinate)

www.niferex.com